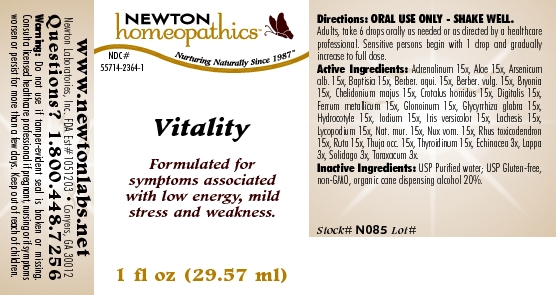 DRUG LABEL: Vitality 
NDC: 55714-2364 | Form: LIQUID
Manufacturer: Newton Laboratories, Inc.
Category: homeopathic | Type: HUMAN OTC DRUG LABEL
Date: 20110301

ACTIVE INGREDIENTS: Epinephrine 15 [hp_X]/1 mL; Aloe 15 [hp_X]/1 mL; Arsenic Trioxide 15 [hp_X]/1 mL; Baptisia Tinctoria 15 [hp_X]/1 mL; Mahonia Aquifolium Root Bark 15 [hp_X]/1 mL; Berberis Vulgaris Root Bark 15 [hp_X]/1 mL; Bryonia Alba Root 15 [hp_X]/1 mL; Chelidonium Majus 15 [hp_X]/1 mL; Crotalus Horridus Horridus Venom 15 [hp_X]/1 mL; Digitalis 15 [hp_X]/1 mL; Iron 15 [hp_X]/1 mL; Nitroglycerin 15 [hp_X]/1 mL; Glycyrrhiza Glabra 15 [hp_X]/1 mL; Centella Asiatica 15 [hp_X]/1 mL; Iodine 15 [hp_X]/1 mL; Iris Versicolor Root 15 [hp_X]/1 mL; Lachesis Muta Venom 15 [hp_X]/1 mL; Lycopodium Clavatum Spore 15 [hp_X]/1 mL; Sodium Chloride 15 [hp_X]/1 mL; Strychnos Nux-vomica Seed 15 [hp_X]/1 mL; Toxicodendron Pubescens Leaf 15 [hp_X]/1 mL; Ruta Graveolens Flowering Top 15 [hp_X]/1 mL; Thuja Occidentalis Leafy Twig 15 [hp_X]/1 mL; Thyroid, Unspecified 15 [hp_X]/1 mL; Echinacea, Unspecified 3 [hp_X]/1 mL; Arctium Lappa Root 3 [hp_X]/1 mL; Solidago Virgaurea Flowering Top 3 [hp_X]/1 mL; Taraxacum Officinale 3 [hp_X]/1 mL
INACTIVE INGREDIENTS: Alcohol

Vitality

INDICATIONS & USAGE SECTION

Vitality Formulated for symptoms associated with low energy, mild stress and weakness.

DOSAGE & ADMINISTRATION SECTION

Directions: ORAL USE ONLY - SHAKE WELL. Adults, take 6 drops orally as needed or as directed by a healthcare professional. Sensitive persons begin with 1 drop and gradually increase to full dose.

OTC - ACTIVE INGREDIENT SECTION

Adrenalinum 15x, Aloe 15x, Arsenicum alb. 15x, Baptisia 15x, Berber. aqui. 15x, Berber. vulg. 15x, Bryonia 15x, Chelidonium majus 15x, Crotalus horridus 15x, Digitalis 15x, Ferrum metallicum 15x, Glonoinum 15x, Glycyrrhiza glabra 15x, Hydrocotyle 15x, Iodium 15x, Iris versicolor 15x, Lachesis 15x, Lycopodium 15x, Nat. mur. 15x, Nux vom. 15x, Rhus toxicodendron 15x, Ruta 15x, Thuja occ. 15x, Thyroidinum 15x, Echinacea 3x, Lappa 3x, Solidago 3x, Taraxacum 3x.

OTC - PURPOSE SECTION

Formulated for symptoms associated with low energy, mild stress and weakness.

INACTIVE INGREDIENT SECTION

Inactive Ingredients: USP Purified Water; USP Gluten-free, non-GMO, organic cane dispensing alcohol 20%

QUESTIONS SECTION

www.newtonlabs.net Newton Laboratories, Inc. FDA Est # 1051203 - Conyers, GA 30012
Questions? 1.800.448.7256

WARNINGS SECTION

Warning: Do not use if tamper - evident seal is broken or missing. Consult a licensed healthcare professional if pregnant, nursing or if symptoms worsen or persist for more than a few days. Keep out of reach of children

OTC - PREGNANCY OR BREAST FEEDING SECTION

Consult a licensed healthcare professional if pregnant, nursing or if symptoms worsen or persist for more than a few days.

OTC - KEEP OUT OF REACH OF CHILDREN SECTION

Keep out of reach of children.